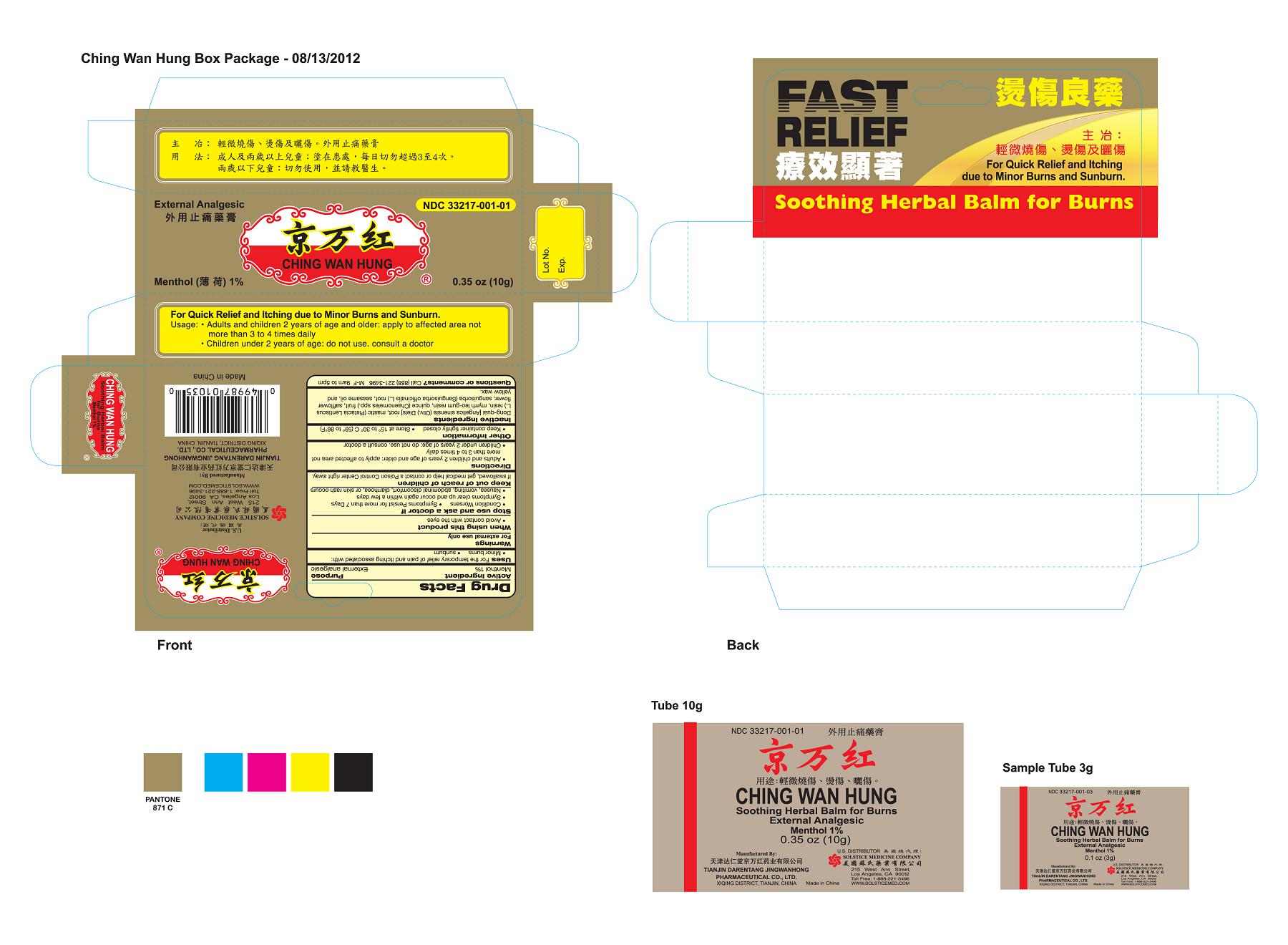 DRUG LABEL: CHING WAN HUNG SOOTHING HERBAL BALM
NDC: 33217-001 | Form: OINTMENT
Manufacturer: TIANJIN DARENTANG JINGWANHONG PHARMACEUTICAL CO., LTD.
Category: otc | Type: HUMAN OTC DRUG LABEL
Date: 20250724

ACTIVE INGREDIENTS: MENTHOL 1 g/100 g
INACTIVE INGREDIENTS: ANGELICA SINENSIS ROOT; PISTACIA LENTISCUS RESIN; MYRRH; QUINCE; SAFFLOWER; SANGUISORBA OFFICINALIS TOP; SESAME OIL; YELLOW WAX

Drug Facts

Active ingredient
Menthol 1%

Purpose
External analgesic

Uses

For the temporary relief of pain and itching associated with:

- minor burns
- sunburn

Warnings
For external use only

When using this product
avoid contact with the eyes

Stop use and ask a doctor if
condition worsens
symptoms persist for more than 7 days
symptoms clear up and occur again within a few days
nausea, vomiting, abdominal discomfort, diarrhea, or skin rash occurs

Keep out of reach of children.
If swallowed, get medical help or contact a Poison Control Center right away.

Directions
adults and children 2 years of age and older: apply to affected area not more than 3 to 4 times daily
children under 2 years of age: do not use, consult a doctor

Other information
keep container tightly closed
store at 15 to 30 C (59 to 86 F)

Inactive ingredients
Dong-quai [Angelica sinensis (Oliv.) Diels] root, mastic (Pistacia Lentiscus L.) resin, myrrh oleo-gum resin, quince (Chaenomeles spp.) fruit, safflower flower,sanguisorba (Sanguisorba officinalis L.) root, sesame oil,and yellow wax.

Questions or comments? Call (888) 221-3496 M-F 9am to 5pm

PACKAGE LABEL

CHING WAN HUNG, Soothing Herbal Balm, External Analgesic, 0.35 oz (10 g), NDC 33217-001-01